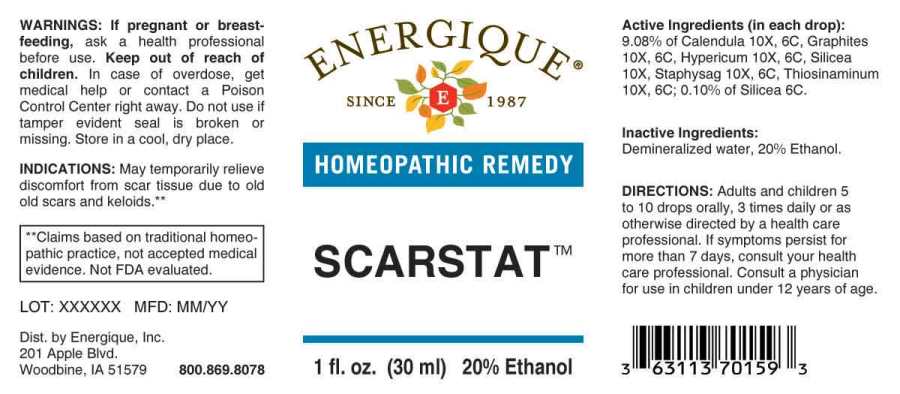 DRUG LABEL: Scarstat
NDC: 44911-0149 | Form: LIQUID
Manufacturer: Energique, Inc.
Category: homeopathic | Type: HUMAN OTC DRUG LABEL
Date: 20241030

ACTIVE INGREDIENTS: CALENDULA OFFICINALIS FLOWERING TOP 10 [hp_X]/1 mL; GRAPHITE 10 [hp_X]/1 mL; HYPERICUM PERFORATUM WHOLE 10 [hp_X]/1 mL; SILICON DIOXIDE 10 [hp_X]/1 mL; DELPHINIUM STAPHISAGRIA SEED 10 [hp_X]/1 mL; ALLYLTHIOUREA 10 [hp_X]/1 mL
INACTIVE INGREDIENTS: WATER; ALCOHOL

DRUG FACTS:

ACTIVE INGREDIENTS:

(in each drop): 9.08% Calendula Officinalis 10X, 6C, Graphites 10X, 6C, Hypericum Perforatum 10X, 6C, Silicea 10X, Staphysagria 10X, 6C, Thiosinaminum 10X, 6C; 0.10% of Silicea 6C.

INDICATIONS:

May temporarily relieve discomfort from scar tissue due to old scars and keloids.**

**Claims based on traditional homeopathic practice, not accepted medical evidence. Not FDA evaluated.

WARNINGS:

If pregnant or breast-feeding, ask a health professional before use.

Keep out of reach of children. In case of overdose, get medical help or contact a Poison Control Center right away.

Do not use if tamper evident seal is broken or missing. Store in a cool, dry place.

Keep out of reach of children. In case of overdose, get medical help or contact a Poison Control Center right away.

DIRECTIONS:

Adults and children 5 to 10 drops orally, 3 time daily or as otherwise directed by a health care professional. If symptoms persist for more than 7 days, consult your health care professional. Consult a physician for use in children under 12 years of age.

INDICATIONS:

For temporary relief of old scar tissue discomfort; scar tissue; old scars; and keloids.**

**Claims based on traditional homeopathic practice, not accepted medical evidence. Not FDA evaluated.

INACTIVE INGREDIENTS:

Demineralized water, 20% Ethanol.

QUESTIONS:

Dist. by Energique, Inc.

201 Apple Blvd

Woodbine, IA 51579 800-869-8078

PACKAGE LABEL DISPLAY:

ENERGIQUE

SINCE 1987

HOMEOPATHIC REMEDY

SCARSTAT

1 fl. oz. (30 ml)